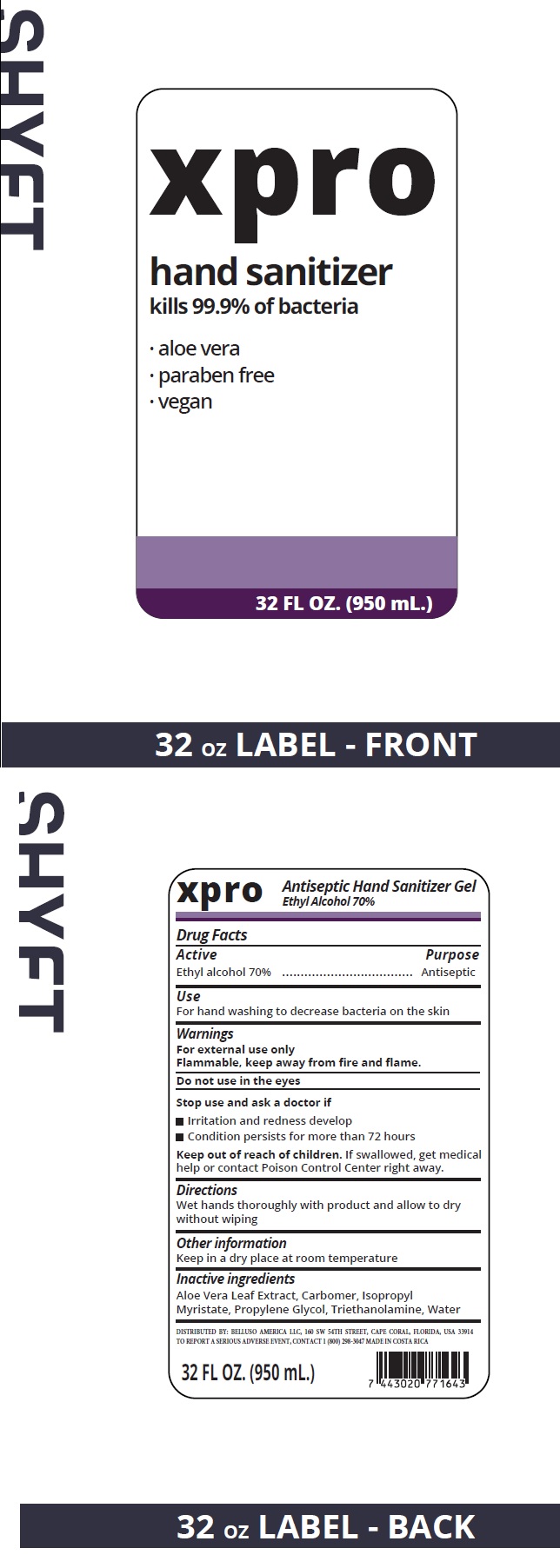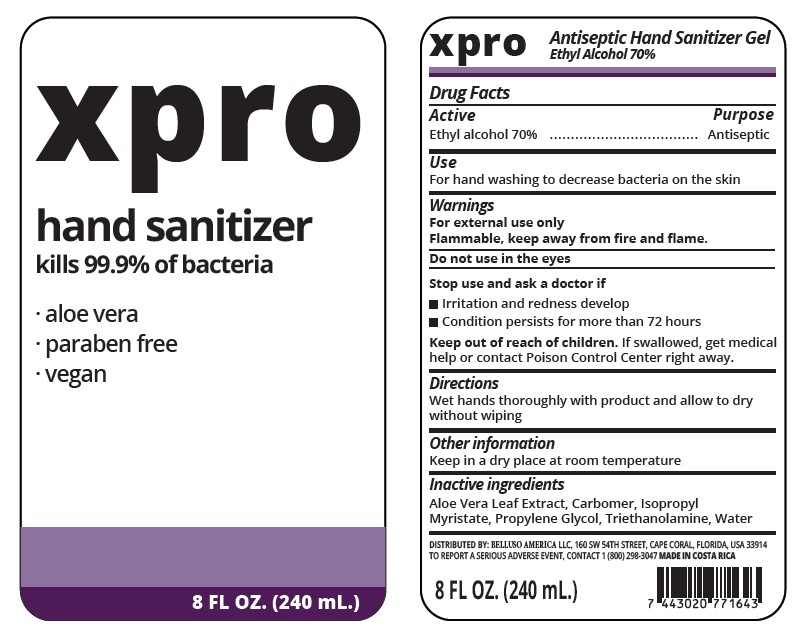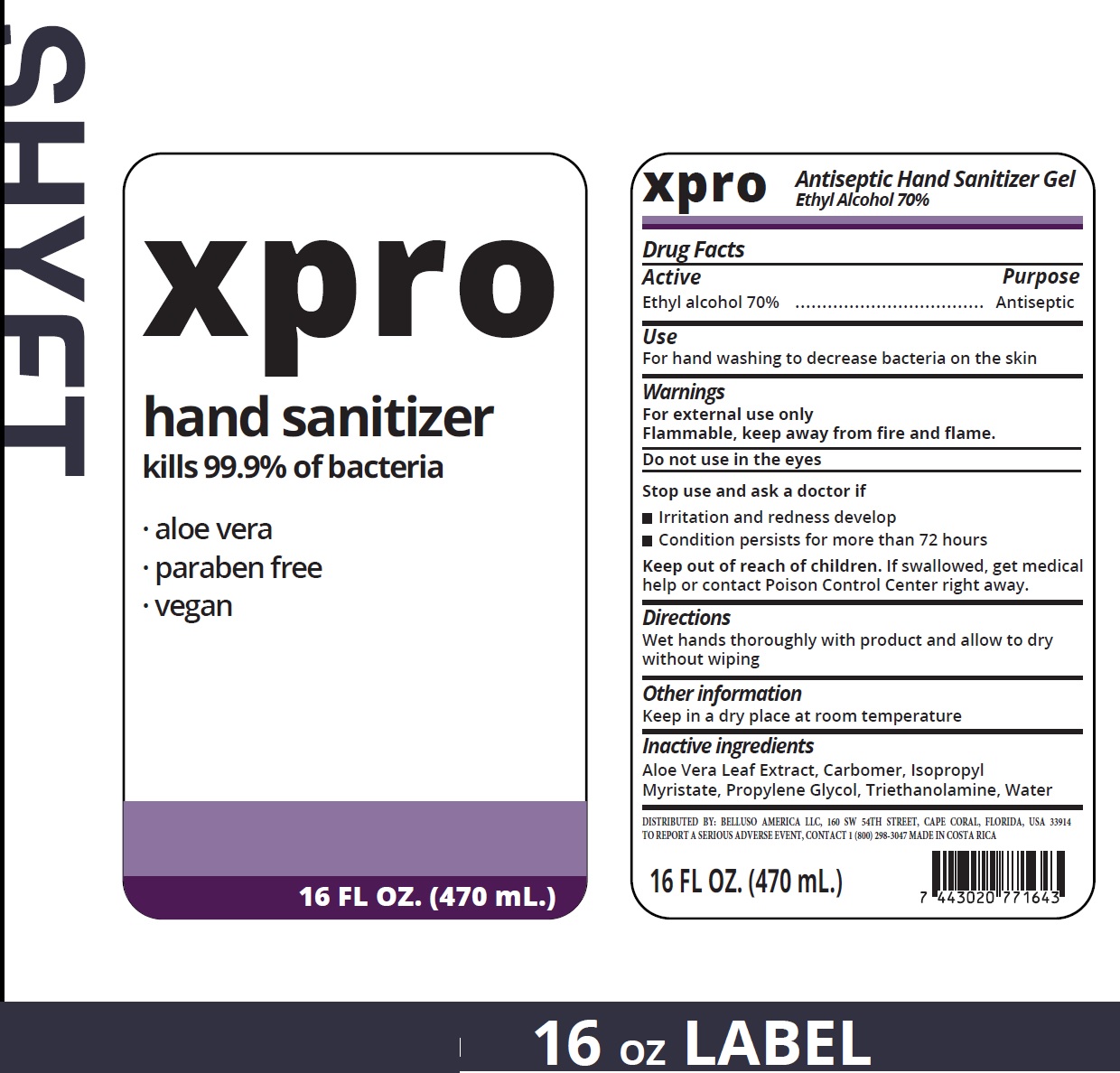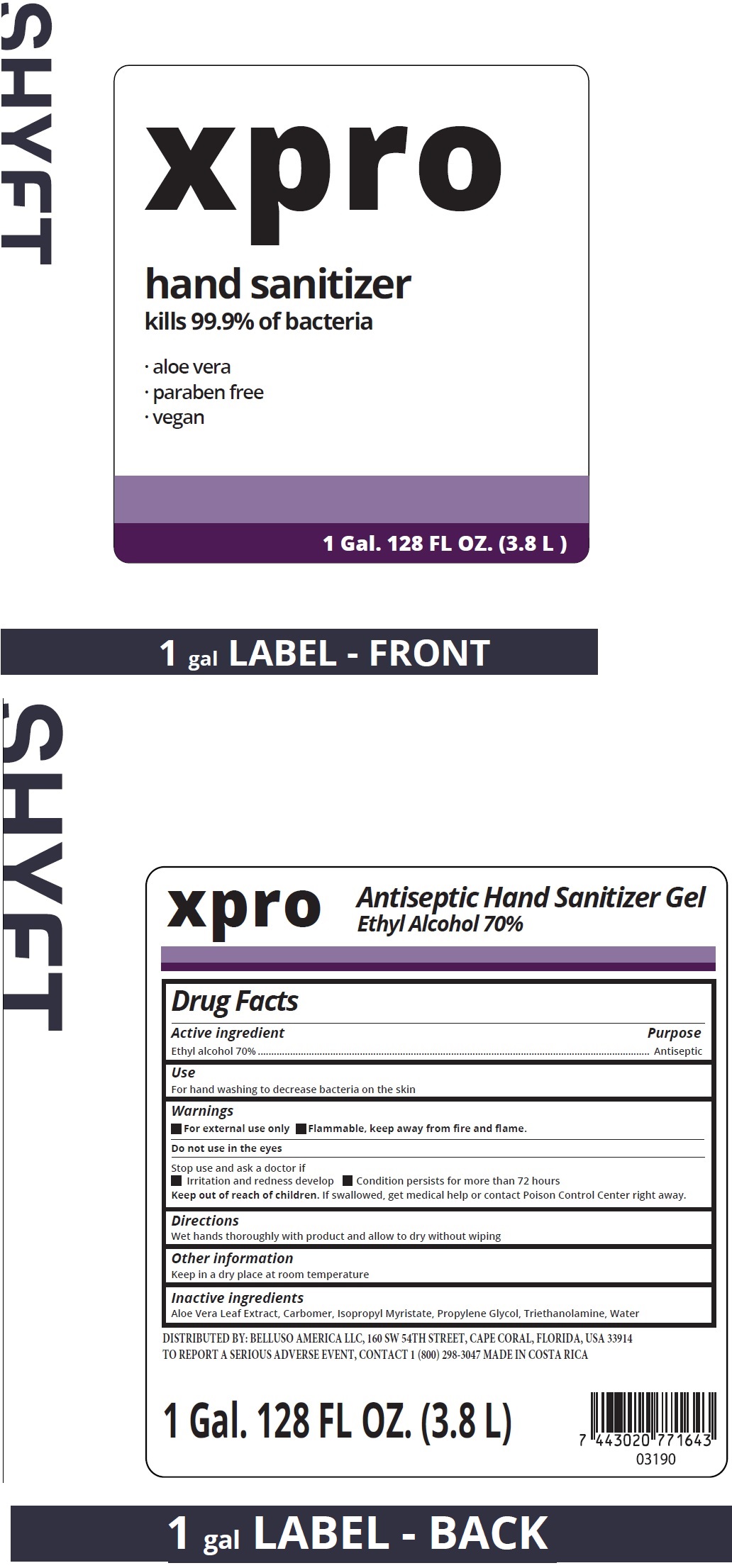 DRUG LABEL: XPRO Antiseptic Hand Sanitizer
NDC: 77939-000 | Form: GEL
Manufacturer: Savone SA
Category: otc | Type: HUMAN OTC DRUG LABEL
Date: 20231212

ACTIVE INGREDIENTS: ALCOHOL 0.7 mL/1 mL
INACTIVE INGREDIENTS: ALOE VERA LEAF; CARBOMER HOMOPOLYMER, UNSPECIFIED TYPE; ISOPROPYL MYRISTATE; PROPYLENE GLYCOL; TROLAMINE; WATER

XPRO Antiseptic Hand Sanitizer Gel

Active

Ethyl alcohol 70%

Purpose

Antiseptic

Use

For hand washing to decrease bacteria on the skin

Warnings

For external use only Flammable, keep away from fire and flame.

Do not use

in the eyes

Stop use and ask a docotor if

- Irritation and redness develop
- Condition persists for more than 72 hours

Keep out of reach of children.

If swallowed, get medical help or contact a Poison Control Center right away.

Directions

Wet hands thoroughly with product and allow to dry without wiping

Other information

Keep in a dry place at room temperature

Inactive ingredients

Aloe Vera Leaf Extract, Carbomer, Isopropyl Myristate, Propylene Glycol, Triethanolamine, Water